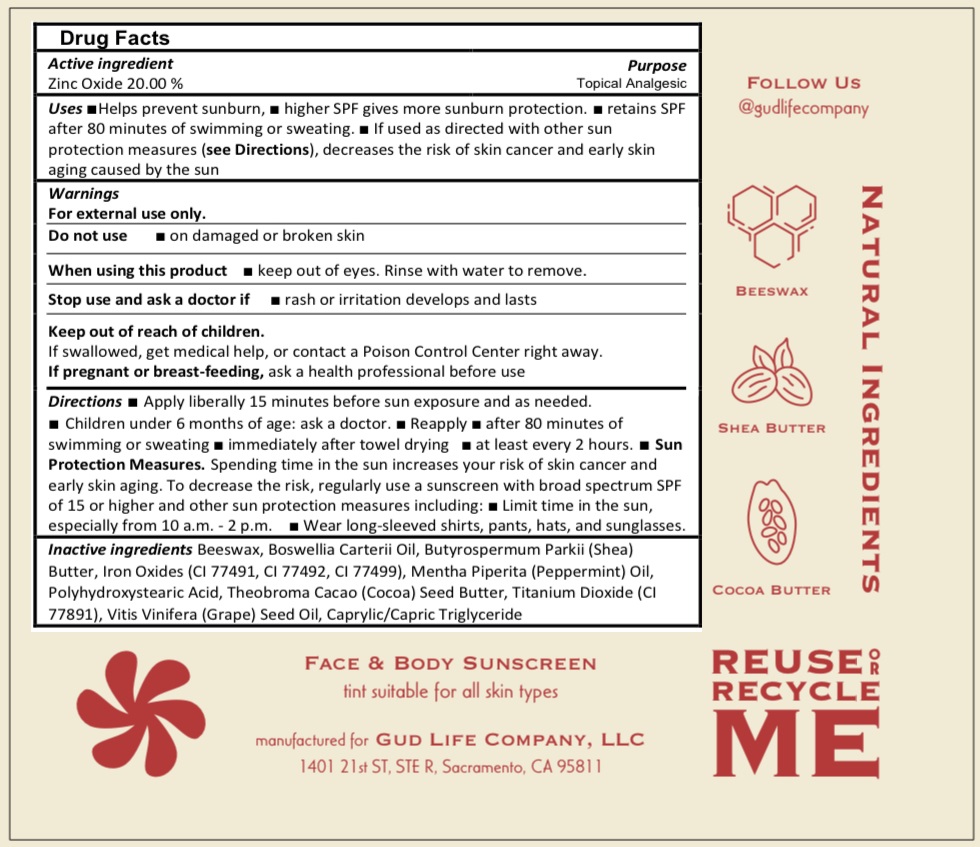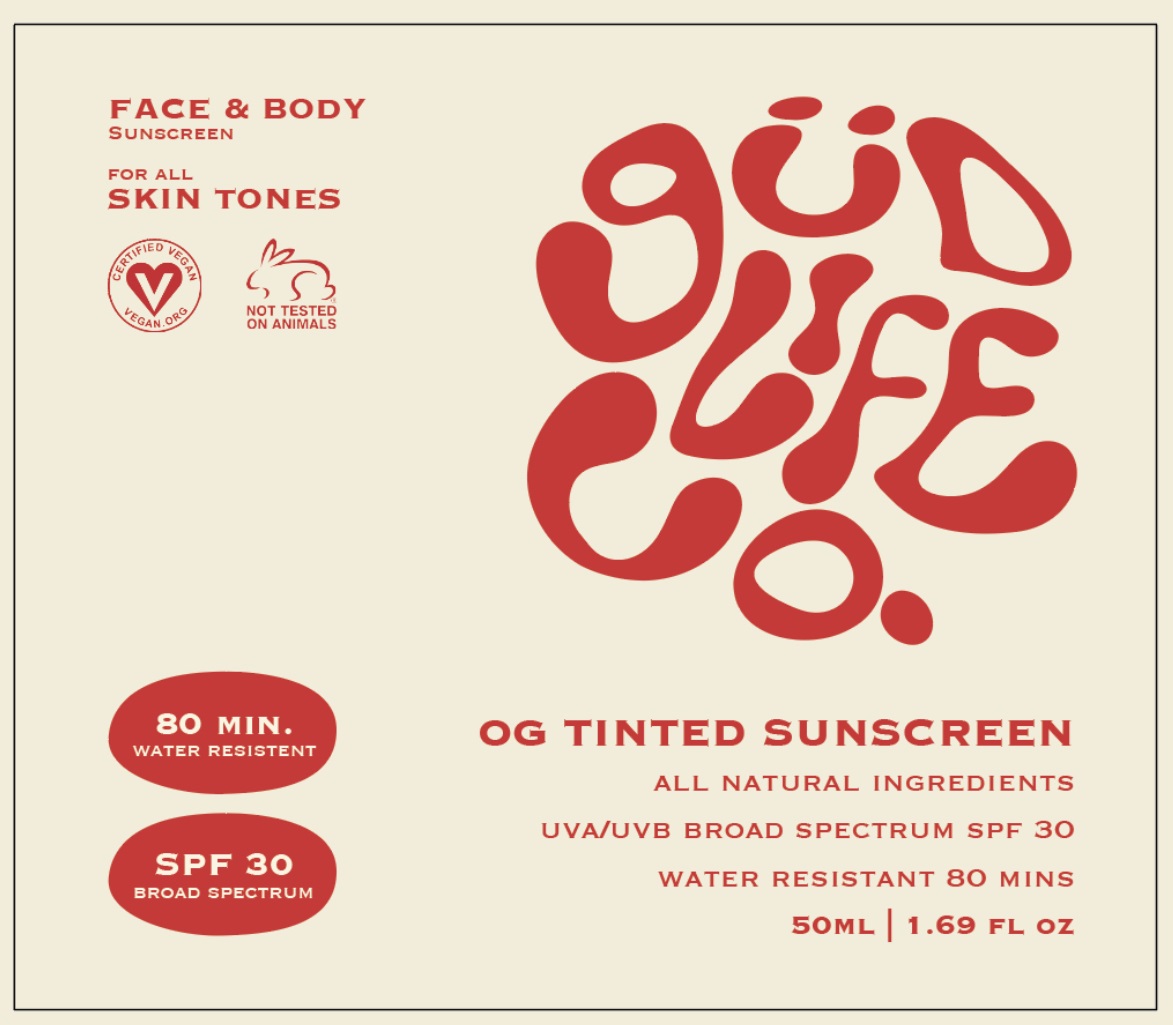 DRUG LABEL: GLC OG Natural Tinted SPF 30 Sunscreen
NDC: 84747-530 | Form: PASTE
Manufacturer: GUD LIFE CO. LLC
Category: otc | Type: HUMAN OTC DRUG LABEL
Date: 20240918

ACTIVE INGREDIENTS: ZINC OXIDE 200 mg/1 mL
INACTIVE INGREDIENTS: YELLOW WAX; FRANKINCENSE OIL; SHEA BUTTER; FERRIC OXIDE RED; FERRIC OXIDE YELLOW; FERROSOFERRIC OXIDE; PEPPERMINT OIL; COCOA BUTTER; TITANIUM DIOXIDE; GRAPE SEED OIL; MEDIUM-CHAIN TRIGLYCERIDES

GLC OG Natural Tinted SPF-30 Sunscreen

Active ingredient

Zinc Oxide 20.00%

Purpose

Topical Analgesic

Uses

- Helps prevent sunburn,
- higher SPF gives more sunburn protection.
- retains SPF after 80 minutes of swimming or sweating.
- If used as directed with other sun protection measures (see Directions), decreases the risk of skin cancer and early skin aging caused by the sun

Warnings

For external use only.

Do not use

- on damaged or broken skin

When using this product

- keep out of eyes. Rinse with water to remove.

Stop use and ask a doctor if

- rash or irritation develops and lasts

Keep out of reach of children.

If swallowed, get medical help, or contact a Poison Control Center right away.

If pregnant or breast-feeding,

ask a health professional before use

Directions

- Apply liberally 15 minutes before sun exposure and as needed.
- Children under 6 months of age: ask a doctor.
- Reapply
- after 80 minutes of swimming or sweating
- immediately after towel drying
- at least every 2 hours.
- Sun Protection Measures.Spending time in the sun increases your risk of skin cancer and early skin aging. To decrease the risk, regularly use a sunscreen with broad spectrum SPF of 15 or higher and other sun protection measures including:
- Limit time in the sun, especially from 10 a.m. - 2 p.m.
- Wear long-sleeved shirts, pants, hats, and sunglasses.

Inactive ingredients

Beeswax, Boswellia Carterii Oil, Butyrospermum Parkii (Shea) Butter, Iron Oxides (CI 77491, CI 77492, CI 77499), Mentha Piperita (Peppermint) Oil, Polyhydroxystearic Acid, Theobroma Cacao (Cocoa) Seed Butter, Titanium Dioxide (CI 77891), Vitis Vinifera (Grape) Seed Oil, Caprylic/Capric Triglyceride